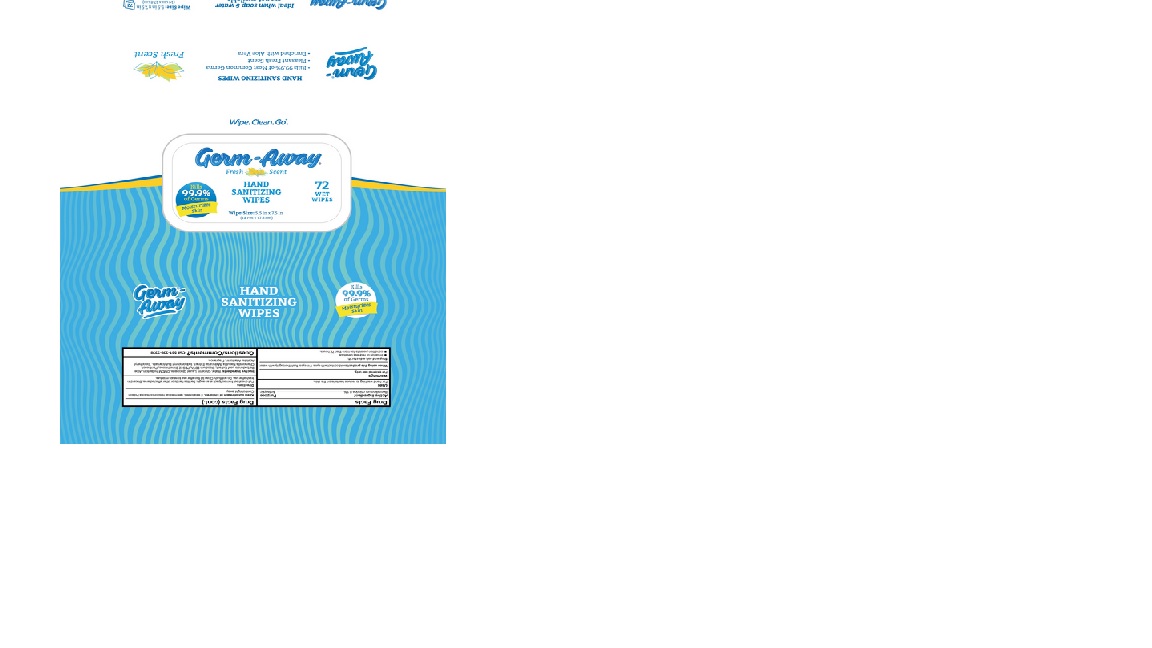 DRUG LABEL: Germ-Away
NDC: 74680-110 | Form: CLOTH
Manufacturer: Unico International Trading Corp
Category: otc | Type: HUMAN OTC DRUG LABEL
Date: 20260108

ACTIVE INGREDIENTS: BENZALKONIUM CHLORIDE 1 mg/1 g
INACTIVE INGREDIENTS: 4-TERT-BUTYLCYCLOHEXYL ACETATE; VIRIDIFLOROL; TETRAHYDROLINALOOL; PANTHENOL; PEG-12 DIMETHICONE (300 CST); .ALPHA.-TOCOPHEROL ACETATE; GLYCERIN; SODIUM HYDROXYMETHYLGLYCINATE; ALLANTOIN; DECYL GLUCOSIDE; EDETATE SODIUM; POTASSIUM SORBATE; SODIUM BENZOATE; CHAMOMILE; WATER; ALOE VERA LEAF; ANHYDROUS CITRIC ACID; 2,2'-OXYDIPROPANOL

Germ-Away

Active Ingredient

Benzalkonium chloride 0.1%

Purpose

Anti-bacterial

Warnings

For external use only. Do not use in the eyes.

Keep out of reach of children, except with adult supervision.

Keep out of eyes. In case of eye contact, rinse with water. If irritation develops, discontinue use. Consult doctor if irritation persists for more than 72 hours.

If swallowed, seek medical attention or contact a Poison Control Center.

Inactive Ingredients

potassium sorbate, sodium hydroxymethylglycinate, aloe vera leaf, anhydrous citric acid, panthenol, water, decyl glucoside, chamomile, allantoin, peg-12 dimethicone, alpha-tocopherol acetate, edetate sodium, glycerin, sodium benzoate, fragrance

Use

For hand washing to decrease bacteria on the skin. May be used on face, arms and legs.

Directions

Pull one sheet from soft pack

Clean hands or affected area and discard

Close lid after each use to keep wipes fresh

Questions

Questions/Comments? Call 561-338-3338

Keep out of the reach of children

Keep out of reach of children, except with adult supervision.